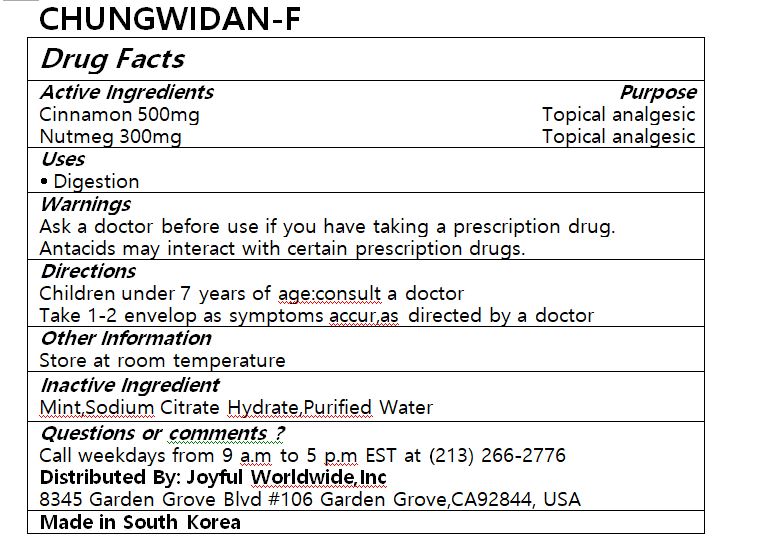 DRUG LABEL: Germ Free ARIA
NDC: 82995-0001 | Form: LIQUID
Manufacturer: Omega Vision Co., Ltd.
Category: otc | Type: HUMAN OTC DRUG LABEL
Date: 20220924

ACTIVE INGREDIENTS: EUCALYPTOL 1.2 g/100 mL
INACTIVE INGREDIENTS: GLYCERIN; WATER

ACTIVE INGREDIENT

cineol, pinene, limonene

PURPOSE

Prevention and treatment of respiratory diseases

Keep out of reach of children

INDICATIONS AND USAGE

1. Connect the liquid cartridge to the main body for electronic control.
2. Inhale through the cartridge inlet slowly to the mouth and bronchi so that the aerosol comes out.
3. When not in use, separate the main body and cartridge, and keep the cartridge closed with a protective cap.

WARNINGS

1. Anyone can use it if there is a consultation and prescription with a doctor.
2. Pregnant women, patients with severe high blood pressure, and people with a constitution allergic to natural fragrances should not use.
3. Do not use if there are side effects such as headache, nausea, vomiting, or seizures after eating health products containing essential oil.

INACTIVE INGREDIENT

distilled water, glycerin, Rb, B,Si, etc.

DOSAGE AND ADMINISTRATION

for oral use